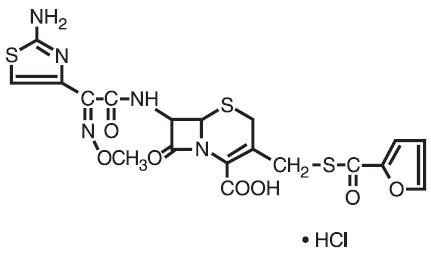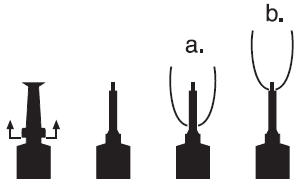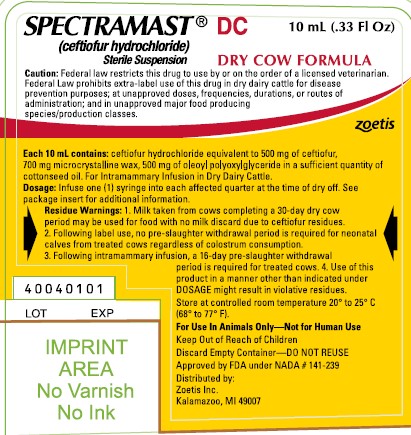 DRUG LABEL: Spectramast
NDC: 54771-5278 | Form: SUSPENSION
Manufacturer: Zoetis Inc.
Category: animal | Type: PRESCRIPTION ANIMAL DRUG LABEL
Date: 20250326

ACTIVE INGREDIENTS: CEFTIOFUR HYDROCHLORIDE 500 mg/10 mL
INACTIVE INGREDIENTS: MICROCRYSTALLINE WAX

SPECTRAMAST® DC

SPECTRAMAST® DC

brand of ceftiofur hydrochloride sterile suspension

For Intramammary Infusion in Dry Dairy Cattle Only

FOR USE IN ANIMALS ONLY — NOT FOR HUMAN USE

CAUTION

Federal law restricts this drug to use by or on the order of a licensed veterinarian. Federal Law prohibits extra-label use of this drug in dry dairy cattle for disease prevention purposes; at unapproved doses, frequencies, durations, or routes of administration; and in unapproved major food producing species/production classes.

DESCRIPTION

Ceftiofur hydrochloride is a cephalosporin antibiotic.

Chemical Structure of Ceftiofur Hydrochloride

U-64279A

Chemical Name of Ceftiofur Hydrochloride

5-Thia-1-azabicyclo[4.2.0]oct-2-ene-2-carboxylic acid, 7 - [[2-(2-amino-4-thiazolyl) - 2 -(methoxyimino)acetyl]amino]-3-[[(2-furanyl-carbonyl)thio]methyl]-8-oxo, hydrochloride.

Ceftiofur Hydrochloride Sterile Suspension is an oil based sterile suspension.

Each 10 mL PLASTET® Disposable Syringe Contains:

Ceftiofur Equivalents (as the hydrochloride salt) | 500 mg
Microcrystalline Wax | 700 mg
Oleoyl Polyoxylglyceride | 500 mg
Cottonseed Oil | q.s.

INDICATIONS FOR USE

SPECTRAMAST® DC Ceftiofur Hydrochloride Sterile Suspension is indicated for the treatment of subclinical mastitis in dairy cattle at the time of dry off associated with Staphylococcus aureus, Streptococcus dysgalactiae, and Streptococcus uberis.

SPECTRAMAST® DC Ceftiofur Hydrochloride Sterile Suspension has been proven effective against Staphylococcus aureus, Streptococcus dysgalactiae, and Streptococcus uberis.

DOSAGE

Infuse one (1) syringe into each affected quarter at the time of dry off.

DIRECTIONS FOR USING THE PLASTET® DISPOSABLE SYRINGE

The syringe is designed to provide the choice of either insertion of the full cannula as has traditionally been practiced, or insertion of no more than 1/8 inch of the cannula, as reported by Eberhart, R.J., et. al. 1987. Current Concepts of Bovine Mastitis, 3rd Edition, National Mastitis Council, Arlington, VA.

a. Full insertion: Remove the red end cap by pulling straight up as shown. Gently insert the full cannula into the teat canal; carefully infuse the product.

b. Partial insertion: Remove the red end cap by pulling straight up as shown. Gently insert the exposed white tip into the teat canal; carefully infuse the product.

ADMINISTRATION

Treatment:

Wash teats thoroughly with warm water containing a suitable dairy antiseptic. Dry teats thoroughly. Milk out udder completely. Using an appropriate antiseptic teat wipe (containing at least 70% isopropyl alcohol), wipe off the end of the affected teat using a separate wipe for each teat. Choose the desired insertion length (full or partial) and insert tip into teat canal; push plunger to dispense entire contents, massage the quarter to distribute the suspension into the milk cistern.

Reinfection:

After successful treatment, reinfection may occur unless good herd management, sanitation, and mechanical safety measures are practiced. Affected cows should be watched carefully to detect recurrence of infection and possible spread to other animals.

CONTRAINDICATIONS

As with all drugs, the use of SPECTRAMAST® DC Sterile Suspension is contraindicated in animals previously found to be hypersensitive to the drug.

Discard Empty Container: DO NOT REUSE

KEEP OUT OF REACH OF CHILDREN

WARNINGS

Penicillins and cephalosporins can cause allergic reactions in sensitized individuals. Topical exposures to such antimicrobials, including ceftiofur, may elicit mild to severe allergic reactions in some individuals. Repeated or prolonged exposure may lead to sensitization. Avoid direct contact of the product with the skin, eyes, mouth and clothing. Sensitization of the skin may be avoided by wearing protective gloves.

Persons with a known hypersensitivity to penicillin or cephalosporins should avoid exposure to this product.

In case of accidental eye exposure, flush with water for 15 minutes. In case of accidental skin exposure, wash with soap and water. Remove contaminated clothing. If allergic reaction occurs (e.g., skin rash, hives, difficult breathing), seek medical attention.

The Safety Data Sheet contains more detailed occupational safety information. For a copy of the Safety Data Sheet or to report adverse reactions, call Zoetis Inc. at 1-888-963-8471. For additional information about adverse drug experience reporting for animal drugs, contact FDA at 1-888-FDA-VETS or at www.fda.gov/reportanimalae.

CONTACT INFORMATION

The Safety Data Sheet contains more detailed occupational safety information. For a copy of the Safety Data Sheet or to report adverse reactions, call Zoetis Inc. at 1-888-963-8471. For additional information about adverse drug experience reporting for animal drugs, contact FDA at 1-888-FDA-VETS or at www.fda.gov/reportanimalae.

RESIDUE WARNINGS

- Milk taken from cows completing a 30-day dry cow period may be used for food with no milk discard due to ceftiofur residues.
- Following label use, no pre-slaughter withdrawal period is required for neonatal calves born from treated cows regardless of colostrum consumption.
- Following intramammary infusion, a 16-day pre-slaughter withdrawal period is required for treated cows.
- Use of this product in a manner other than indicated under DOSAGE might result in violative residues.

CLINICAL MICROBIOLOGY

Ceftiofur is a broad-spectrum cephalosporin antibiotic that exerts its effect by inhibiting bacterial cell wall synthesis. Like other ß-lactam antimicrobial agents, the cephalosporins inhibit cell wall synthesis by interfering with the enzymes essential for peptidoglycan synthesis. This effect results in lysis of the bacterial cell and accounts for the bactericidal nature of these agents. Ceftiofur has demonstrated in vitro activity against clinical isolates and isolates from diagnostic laboratories. The results of susceptibility testing of these isolates against ceftiofur are presented in Tables 1 and 2. Appropriate reference strains were also susceptibility tested and their minimum inhibitory concentration (MIC) values and zone of inhibition with a 30 μg disk are presented in Table 4.

Table 1. Ceftiofur MIC values for isolates from a multi-site clinical field study evaluating subclinical mastitis in dry dairy cows in the U.S. during 2000
Organism | No. | MIC90 [The MIC for 90% of the isolates.] (μg/mL) | MIC range (μg/mL)
Staphylococcus aureus | 300 | 1.0 | ≤0.06 to 2.0
Streptococcus dysgalactiae | 55 | ≤0.06 | ≤0.06 to >64.0
Streptococcus uberis | 58 | 1.0 | ≤0.06 to 4.0

* The MIC for 90% of the isolates.Table 2. Ceftiofur MIC values [The above in vitro data are available, but their clinical significance is unknown.] for mastitis pathogens from diagnostic laboratories in the U.S. and Canada
Organism | No. | Date isolated | MIC90 [The MIC for 90% of the isolates.] (μg/mL) | MIC range (μg/mL)
Staphylococcus aureus | 135 | 1991–1992 | 1.0 | 0.13 to 2.0
Staphylococcus aureus | 10 | 1993 | 1.0 | 0.25 to 1.0
Staphylococcus aureus | 107 | 1995 | 1.0 | 0.25 to 2.0
Staphylococcus aureus | 61 | 2000 | 1.0 | ≤0.06 to 2.0
Coagulase (-) staphylococci | 139 | 2000–2001 | 1.0 | ≤0.06 to 2.0
Streptococcus dysgalactiae | 15 | 1991–1992 | 1.0 | ≤0.06 to 2.0
Streptococcus dysgalactiae | 15 | 1993 | ≤0.0039 | No range [No range, all isolates yielded the same value.]
Streptococcus dysgalactiae | 152 | 1997–1999 | 0.25 | 0.25 to 4.0
Streptococcus dysgalactiae | 64 | 2000 | ≤0.06 | ≤0.06 to 0.5
Streptococcus uberis | 22 | 1991–1992 | 0.5 | ≤0.06 to 4.0
Streptococcus uberis | 15 | 1993 | 0.03 | ≤0.0039 to 0.06
Streptococcus uberis | 133 | 1997–1999 | 0.5 | 0.5 to 8.0
Streptococcus uberis | 20 | 2000 | 1.0 | <0.06 to 2.0
Escherichia coli | 39 | 1991–1992 | 1.0 | 0.25 to 1.0
Escherichia coli | 40 | 1993 | 0.5 | 0.13 to 1.0
Escherichia coli | 52 | 2000 | 0.5 | ≤0.06 to 1.0

* The above in vitro data are available, but their clinical significance is unknown.
** The MIC for 90% of the isolates.
† No range, all isolates yielded the same value.

Based on pharmacokinetic, milk residue and clinical effectiveness studies in dairy cattle following intramammary infusion of ceftiofur and the MIC and disk (30 μg) diffusion data from mastitis pathogens, the following breakpoints are recommended by the National Committee for Clinical Laboratory Standards [now the Clinical and Laboratories Standards Institute (CLSI)] (Table 3).

Table 3. Current recommended interpretive criteria established by CLSI for ceftiofur for Bovine Mastitis
Bovine Mastitis Organisms | Disk Content | Zone Diameter (mm) |  |  | MIC breakpoint (μg/mL)
Bovine Mastitis Organisms | Disk Content | S | I | R | S | I | R
Staphylococcus aureus
Streptococcus dysgalactiae
Streptococcus uberis | 30 μg | ≥21 | 18–20 | ≤17 | ≤2.0 | 4.0 | ≥8.0
Streptococcus agalactiae
Escherichia coli
S – Susceptible
I – Intermediate
R – Resistant

Standardized procedures require the use of laboratory control organisms for both standardized diffusion techniques and standardized dilution techniques. The 30 μg ceftiofur sodium disk should give the following zone diameters and the ceftiofur sodium standard reference powder (or disk) should provide the following MIC values for the reference strain. The ceftiofur sodium disks or standard reference powder is appropriate for ceftiofur hydrochloride (Table 4).

S – Susceptible
I – Intermediate
R – Resistant

Table 4. Acceptable quality control ranges for ceftiofur against CLSI recommended American Type Culture Collection (ATCC) reference strains
Organism (ATCC No.) | Zone Diameter [All testing performed using a 30 μg disk.] (mm) | MIC range (μg/mL)
Escherichia coli (25922) | 26 to 31 | 0.25 to 1.0
Staphylococcus aureus (29213) | --- | 0.25 to 1.0
Staphylococcus aureus (25923) | 27 to 31 | ---
Pseudomonas aeruginosa (27853) | 14 to 18 | 16.0 to 64.0

*All testing performed using a 30 μg disk.

EFFECTIVENESS

The effectiveness of a single intramammary (IMM) infusion of ceftiofur hydrochloride for the treatment of subclinical mastitis present at the time of dry off was demonstrated in a randomized block design study. Nineteen veterinary investigators enrolled cows in 21 herds and from these 21 herds, 431 cows and 1708 quarters met enrollment criteria in the study and calved within a 45 to 60 day period following enrollment. The enrollment criteria were whole udder somatic cell counts greater than 400,000 cells/mL or a linear somatic cell count score greater than or equal to 5. Milk microbiologic samples were obtained prior to treatment and at Days 3 and 5 post-calving. There were 5 treatment groups including a negative control group. There were 43 cows in the negative control group and 51 cows in the 500 mg ceftiofur group that had a positive pre-treatment milk culture that were evaluated for treatment success. The primary decision variable was the microbiologic (therapeutic) cure in which bacteria isolated pre-treatment were absent from both posttreatment samples.

In another study in eleven study herds, 446 cows with a somatic cell count (SCC) greater than or equal to 400,000 cells/mL or a linear score greater than or equal to 5 were enrolled. Cows with a dry period of at least 45 days were blocked by lactation (1st + 2nd or ≥3rd). A single quarter milk sample was aseptically obtained from all four quarters for bacterial culture prior to treatment and on Days 3 and 5 post-calving. There were 4 treatment groups including a negative control. There were 84 cows in the negative control and 73 in the 500 mg ceftiofur group that had a positive pre-treatment milk culture that were evaluated for treatment success. The primary decision variable was the microbiologic (therapeutic) cure in which bacteria isolated pre-treatment were absent from both post-treatment samples.

Ceftiofur was found to be effective against Staphylococcus aureus, Streptococcus dysgalactiae, and Streptococcus uberis, when compared to negative controls. This intramammary ceftiofur formulation was well tolerated. No adverse formulation related events were noted during the entire study. A large multi-location field dose confirmation study and a pilot study demonstrated that 500 mg of ceftiofur infused once per quarter at the time of dry off was effective for the treatment of subclinical mastitis in dairy cattle at the time of dry off.

ANIMAL SAFETY

An udder irritation study was conducted in 22 healthy lactating dairy cows to assess udder irritation following a single intramammary infusion of a sterile oil-based suspension containing 500 mg of ceftiofur into all four quarters followed by milk-out 12 hours later. Throughout the 10 day post-treatment observation period there was a clinically insignificant rise in SCC to mean levels <200,000 cells/mL from the pre-infusion level of <69,000 cells/mL. No clinical signs of udder irritation (swelling, pain, or redness), changes in rectal temperature, or changes in milk production were noted in this study. Clinical observations were made during a GLP residue depletion study of 36 cows following a single intramammary infusion of a sterile oil based suspension containing 500 mg of ceftiofur into all four quarters at the end of lactation. No report of udder irritation or adverse reaction was noted in the daily visual observations over the 14 days immediately following treatment. Collectively, these studies demonstrate that the intramammary infusion of an oil-based sterile suspension containing 500 mg of ceftiofur once into all four quarters at the end of lactation is clinically safe and non-irritating to the udder of non-lactating dairy cows.

MILK AND TISSUE RESIDUE DEPLETION

A metabolism study in cattle using radiolabeled ceftiofur provided the data to establish tolerances for ceftiofur-related residues (as desfuroylceftiofur) in tissue and milk. These tolerances of ceftiofur residues are 0.1 ppm in milk, 0.4 ppm in kidney, 2.0 ppm in liver, and 1.0 ppm in muscle.

Pivotal residue decline studies were conducted to assess the depletion of ceftiofur-related residues, measured as desfuroylceftiofur using the official analytical method, in tissues of treated cows, in milk from treated cows, and in tissues of calves born to treated cows. In these studies, non-mastitic cows received 500 mg of ceftiofur per quarter into all four quarters once at dry off. The milk residue depletion study demonstrated that milk produced at calving may be used for human consumption with no discard period when the treatment to calving interval is 30 days or more. The tissue depletion study measured residues in the tissues of treated cows and in the tissues of neonatal calves born to treated cows. In neonatal calves born to treated cows, tissue residues were less than the codified tolerances for kidney, liver and muscle. These data support a zero day pre-slaughter withdrawal period for calves born to treated cows when the treatment to calving interval is 30 days or more, regardless of colostrum consumption. The tissue residue depletion data support a 16-day pre-slaughter withdrawal period following intramammary infusion for treated cows.

STORAGE CONDITIONS

Store at controlled room temperature 20° to 25° C (68° to 77° F). Protect from light. Store plastets in carton until used.

HOW SUPPLIED

SPECTRAMAST® DC Sterile Suspension is available in cartons containing 1 unbroken package of 12–10 mL PLASTET® Disposable Syringes and in pails containing 12 unbroken packages of 12-10 mL PLASTET® Disposable Syringes.

Approved by FDA under NADA # 141-239
zoetis
Distributed by:
Zoetis Inc.
Kalamazoo, MI 49007
www.spectramast.com or call 1-888-963-8471
Revised: December 2022

40040100

PRINCIPAL DISPLAY PANEL - 12 Syringe Carton

40040101